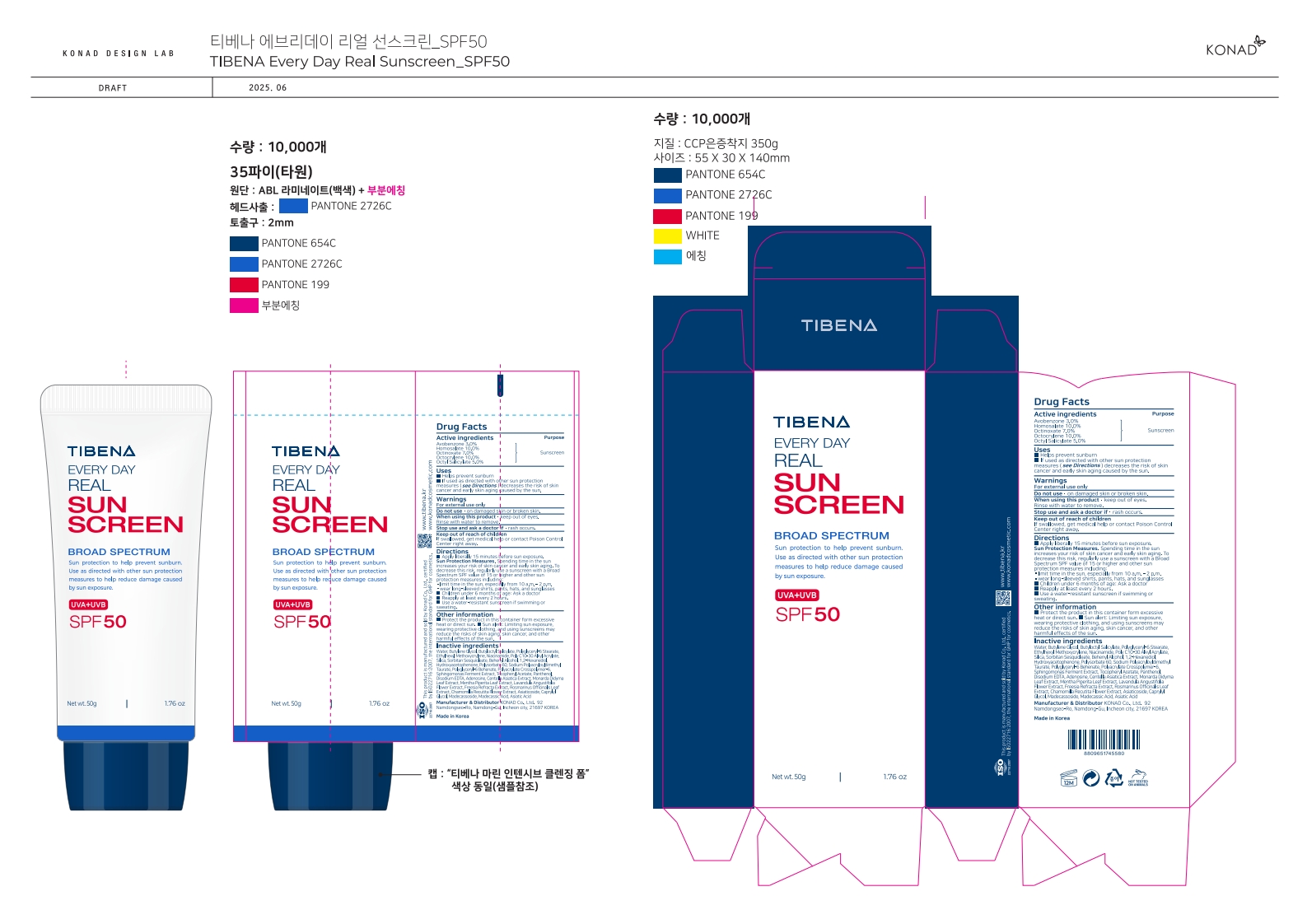 DRUG LABEL: TIBENA EVERY DAY REAL SUNSCREEN SPF50
NDC: 74740-460 | Form: CREAM
Manufacturer: KONAD CO LTD
Category: otc | Type: HUMAN OTC DRUG LABEL
Date: 20250622

ACTIVE INGREDIENTS: OCTINOXATE 3.5 g/50 g; HOMOSALATE 5 g/50 g; OCTOCRYLENE 5 g/50 g; ETHYLHEXYL SALICYLATE 2.5 g/50 g; AVOBENZONE 1.5 g/50 g
INACTIVE INGREDIENTS: PANTHENOL; MONARDA DIDYMA LEAF; ROSEMARY; MADECASSOSIDE; POLYGLYCERYL-6 STEARATE; SILICA; CENTELLA ASIATICA TRITERPENOIDS; ETHYLHEXYL METHOXYCRYLENE; NIACINAMIDE; WATER; BUTYLENE GLYCOL; BUTYLOCTYL SALICYLATE; BEHENYL ALCOHOL; SODIUM POLYACRYLOYLDIMETHYL TAURATE; POLYGLYCERYL-6 BEHENATE; POLYACRYLATE CROSSPOLYMER-6; ALPHA-TOCOPHEROL ACETATE; ASIATICOSIDE; ADENOSINE; SORBITAN SESQUIOLEATE; 1,2-HEXANEDIOL; HYDROXYACETOPHENONE; POLYSORBATE 60; MADECASSIC ACID

KONAD CO LTD_TIBENA EVERY DAY REAL SUN BLOCK

Active ingredients

Avobenzone 3.0%

Homosalate 10.0%

Octinoxate 7.0%

Octocrylene 10.0%

Octyl Salicylate 5.0%

Purpose

sunscreen

Uses

• helps prevent sunburn

• if used as directed with other sun protection measures (see Directions) decreases the risk of skin cancer and early skin aging caused by the sun.

Warnings

For external use only

Do not use

· on damaged skin or broken skin.

When using this product

· keep out of eyes. Rinse with water to remove.

Stop use and ask a doctor if

· rash occurs.

Keep out of reach of children

If swallowed, get medical help or contact Poison Control Center right away.

Directions

■ Apply liberally 15 minutes before sun exposure.
Sun Protection Measures. Spending time in the sun increases your risk of skin cancer and early skin aging. To decrease this risk, regularly use a sunscreen with a Broad Spectrum SPF value of 15 or higher and other sun protection measures including:
·limit time in the sun, especially from 10 a.m. – 2 p.m.
·wear long-sleeved shirts, pants, hats, and sunglasses
■ Children under 6 months of age: Ask a doctor
■ Reapply at least every 2 hours.
■ Use a water-resistant sunscreen if swimming or sweating.

Other information

■ Protect the product in this container form excessive heat or direct sun. ■ Sun alert: Limiting sun exposure, wearing protective clothing, and using sunscreens may reduce the risks of skin aging, skin cancer, and other harmful effects of the sun.

Inactive ingredients

Water, Butylene Glycol, Butyloctyl Salicylate, Polyglyceryl-6 Stearate, Ethylhexyl Methoxycrylene, Niacinamide, Poly C10-30 Alkyl Acrylate, Silica, Sorbitan Sesquioleate, Behenyl Alcohol, 1,2-Hexanediol, Hydroxyacetophenone, Polysorbate 60, Sodium, Polyacryloyldimethyl Taurate, Polyglyceryl-6 Behenate, Polyacrylate Crosspolymer-6, Sphingomonas Ferment Extract, Tocopheryl Acetate, Panthenol, Disodium EDTA, Adenosine, Centella Asiatica Extract, Monarda Didyma Leaf Extract, Mentha Piperita Leaf Extract, Lavandula Angustifolia Flower Extract, Freesia Refracta Extract, Rosmarinus Officinalis Leaf Extract, Chamomilla Recutita Flower Extract, Asiaticoside, Caprylyl Glycol, Madecassoside, Madecassic Acid, Asiatic Acid